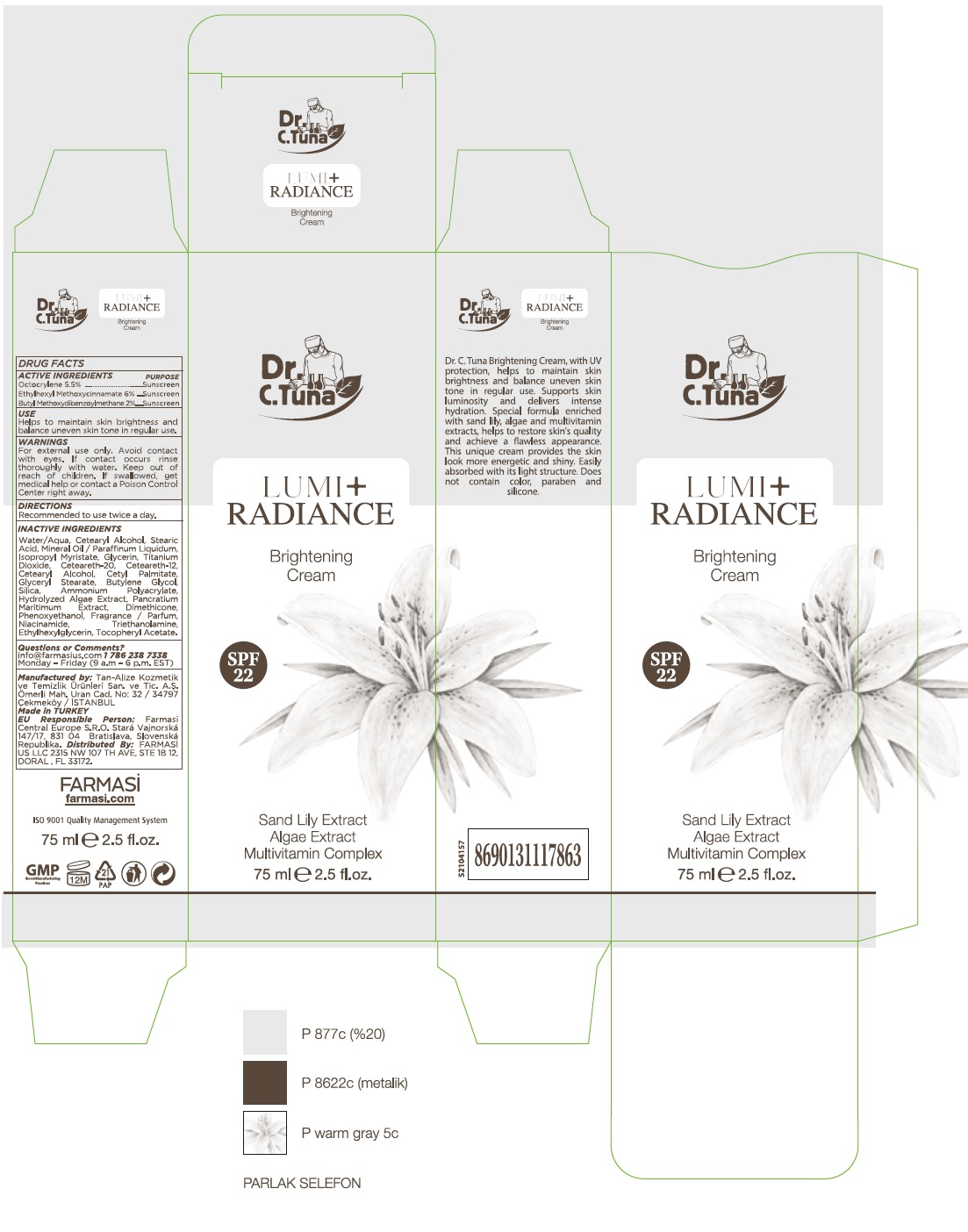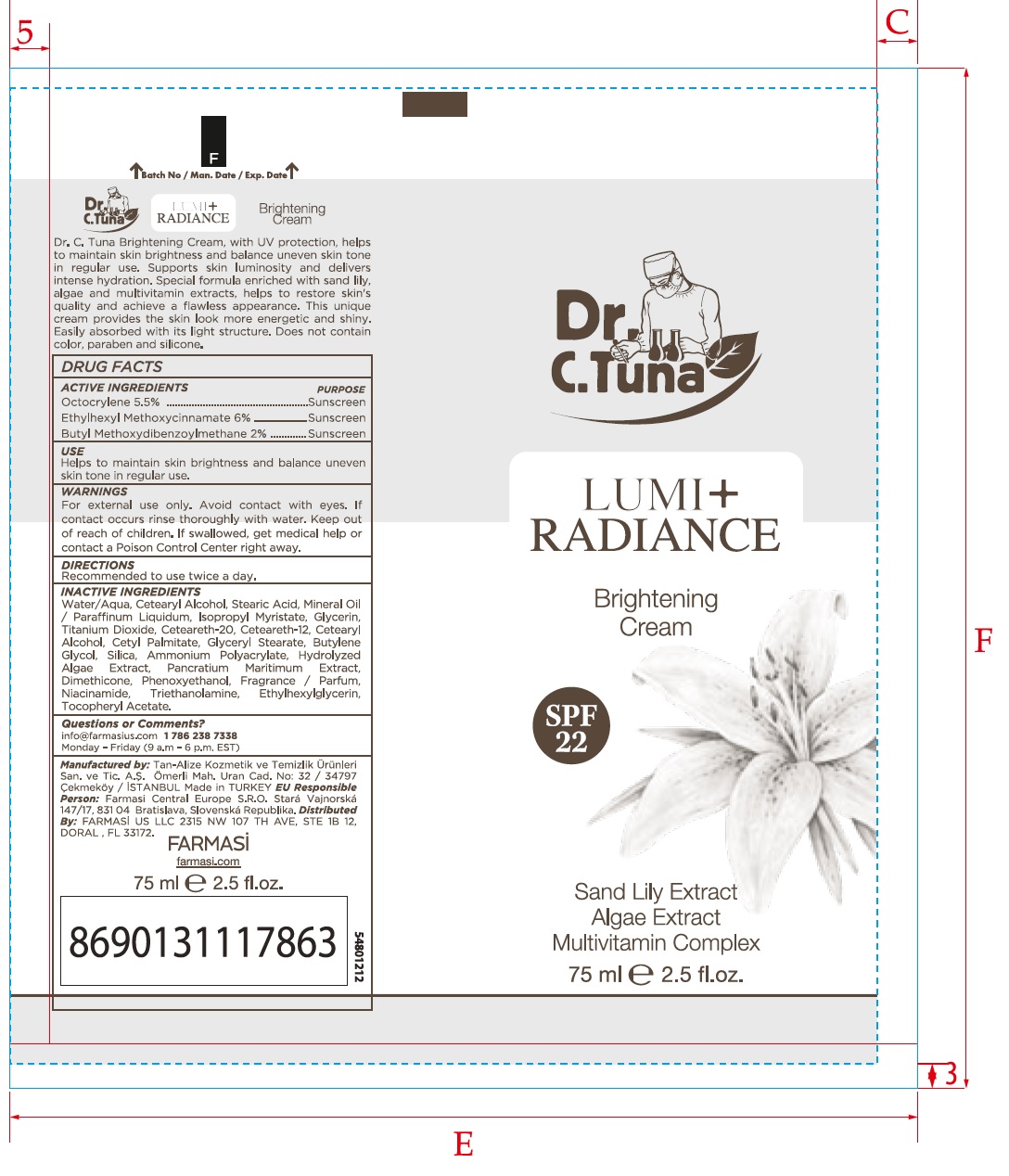 DRUG LABEL: Dr. C. Tuna Lumi Radiance Brightening
NDC: 74690-003 | Form: CREAM
Manufacturer: Farmasi US LLC
Category: otc | Type: HUMAN OTC DRUG LABEL
Date: 20260109

ACTIVE INGREDIENTS: OCTOCRYLENE 55 mg/1 mL; OCTINOXATE 60 mg/1 mL; AVOBENZONE 20 mg/1 mL
INACTIVE INGREDIENTS: WATER; CETOSTEARYL ALCOHOL; STEARIC ACID; MINERAL OIL; ISOPROPYL MYRISTATE; GLYCERIN; TITANIUM DIOXIDE; POLYOXYL 20 CETOSTEARYL ETHER; CETEARETH-12; CETYL PALMITATE; GLYCERYL MONOSTEARATE; BUTYLENE GLYCOL; SILICON DIOXIDE; DIMETHICONE; PHENOXYETHANOL; NIACINAMIDE; ETHYLHEXYLGLYCERIN; .ALPHA.-TOCOPHEROL ACETATE

Dr. C. Tuna Lumi Radiance Brightening Cream

ACTIVE INGREDIENTS

Octocrylene 5.5%

Ethylhexyl Methoxycinnamate 6%

Butyl Methoxydibenzoylmethane 2%

PURPOSE

Sunscreen

USE

Helps to maintain skin brightness and balance uneven skin tone in regular use.

WARNINGS

For external use only. Avoid contact with eyes. If contact occurs rinse thoroughly with water.

Keep out of reach of children. If swallowed, get medical help or contact a Poison Control Center right away.

DIRECTIONS

Recommended to use twice a day.

INACTIVE INGREDIENTS

Water/Aqua, Cetearyl Alcohol, Stearic Acid, Mineral Oil / Paraffinum Liquidum, Isopropyl Myristate, Glycerin, Titanium Dioxide, Ceteareth-20, Ceteareth-12, Cetearyl Alcohol, Cetyl Pamitate, Glyceryl Stearate, Butylene Glycol, Silica, Ammonium Polyacrylate, Hydrolyzed Algae Extract, Pancratium Maritimum Extract, Dimethicone, Phenoxyethanol, Fragrance / Parfum, Niacinamide, Triethanolamine, Ethylhexylglycerin, Tocopheryl Acetate.

Questions or Comments?

info@farmasius.com 1 786 238 7338

Monday - Friday (9 a.m - 6 p.m. EST)

Manufactured by: Tan-Alize Kozmetik ve Temizlik Ürünleri San. ve. Tic. A.S. Ömerli Mah. Uran Cad. No: 32 / 34797 Cekmeköy / ISTANBUL

Made in TURKEY

EU REsponsible Person: Farmasi Central Europe S.R.O. Stará Vajnorská Republika. Distributed By: FARMASI US LLC 2315 NW 107 TH AVE, STE 1B 12, DORAL , FL 33172.